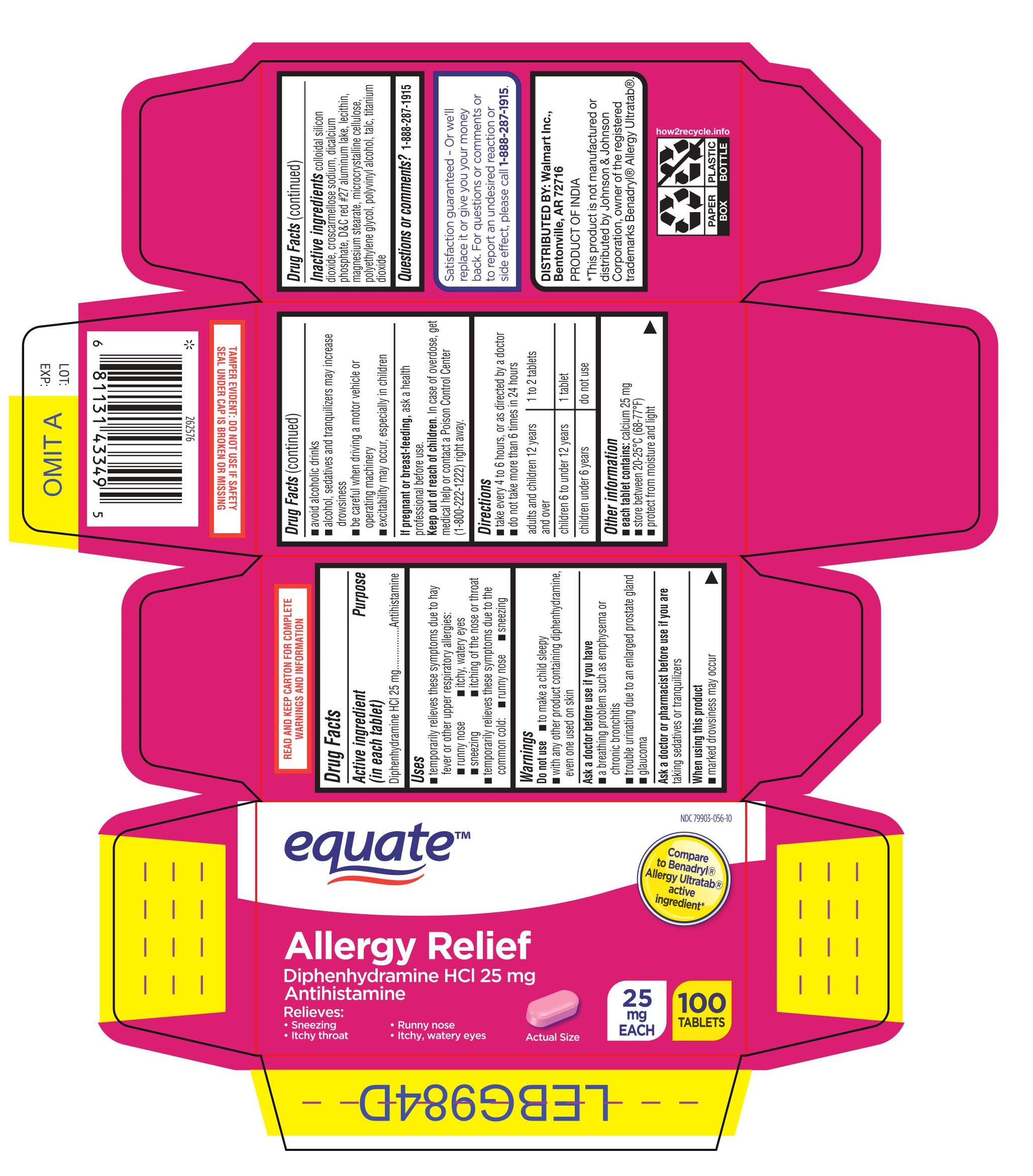 DRUG LABEL: ALLERGY RELIEF
NDC: 79903-056 | Form: TABLET, FILM COATED
Manufacturer: Wal-Mart Stores Inc
Category: otc | Type: HUMAN OTC DRUG LABEL
Date: 20260126

ACTIVE INGREDIENTS: DIPHENHYDRAMINE HYDROCHLORIDE 25 mg/1 1
INACTIVE INGREDIENTS: CROSCARMELLOSE SODIUM; D&C RED NO. 27; SILICON DIOXIDE; ANHYDROUS DIBASIC CALCIUM PHOSPHATE; LECITHIN, SOYBEAN; MAGNESIUM STEARATE; MICROCRYSTALLINE CELLULOSE; POLYVINYL ALCOHOL, UNSPECIFIED; POLYETHYLENE GLYCOL, UNSPECIFIED; TALC; TITANIUM DIOXIDE; WATER

Equate ALLERGY RELIEF Tablets

Drug Facts

Active ingredient (in each tablet)

Diphenhydramine HCl 25 mg

Purpose

Antihistamine

Uses

- temporarily relieves these symptoms due to hay fever or other upper respiratory allergies:
  - runny nose
  - itchy, watery eyes
  - sneezing
  - itching of the nose or throat
- temporarily relieves these symptoms due to the common cold:
  - runny nose
  - sneezing

Warnings

Do not use

- to make a child sleepy
- with any other product containing diphenhydramine, even one used on skin

Ask a doctor before use if you have

- a breathing problem such as emphysema or chronic bronchitis
- trouble urinating due to an enlarged prostate gland
- glaucoma

Ask a doctor or pharmacist before use if you are taking sedatives or tranquilizers

When using this product

- marked drowsiness may occur
- avoid alcoholic drinks
- alcohol, sedatives and tranquilizers may increase drowsiness
- be careful when driving a motor vehicle or operating machinery
- excitability may occur, especially in children

PREGNANCY OR BREAST FEEDING

If pregnant or breast-feeding, ask a health professional before use.

Keep out of reach of children. In case of overdose, get medical help or contact a Poison Control Center right away. 1(800)222-1222

Directions

- take every 4 to 6 hours or as directed by a doctor
- do not take more than 6 times in 24 hours

adults and children 12 years of age and over | 1 to 2 tablets
children 6 to under 12 years of age | 1 tablet
children under 6 years of age | do not use this product in children under 6 years of age

Other information

- each tablet contains: calcium 25 mg
- store at controlled room temperature 20°-25°C (68°-77°F)
- protect from moisture and light
- see end flap for expiration date and lot number

Inactive ingredients

colloidal silicon dioxide, croscarmellose sodium, D&C red No 27, dicalcium phosphate, lecithin, magnesium stearate, microcrystalline cellulose, polyethylene glycol, polyvinyl alcohol, talc, titanium dioxide

Questions or comments?

1-888-287-1915